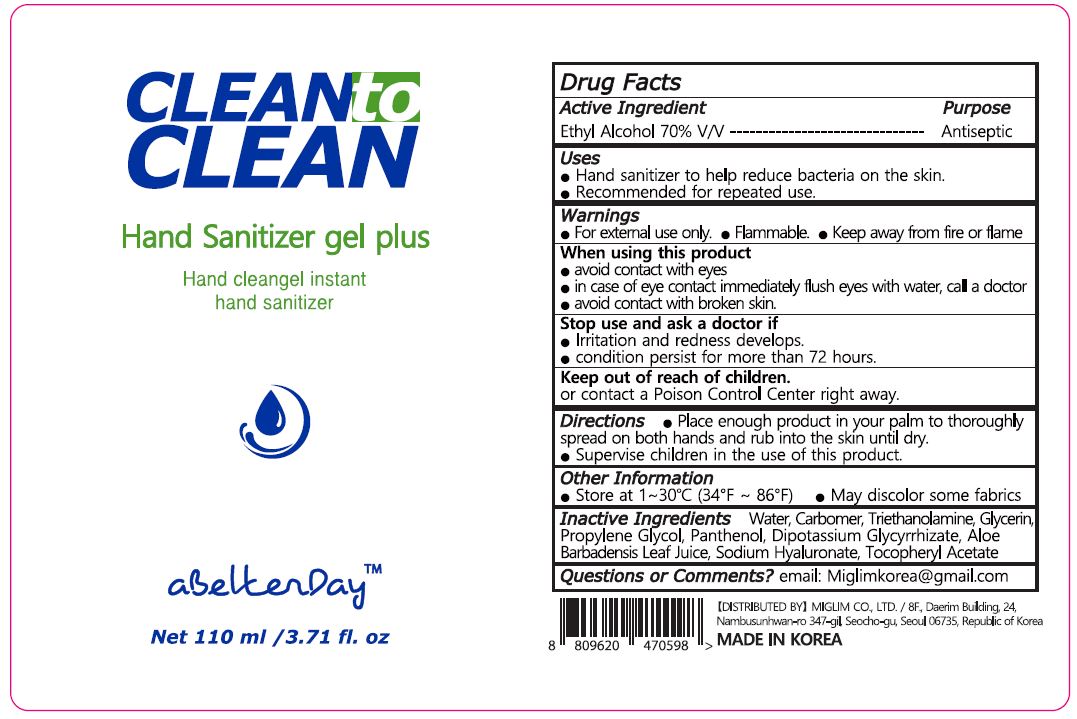 DRUG LABEL: CLEAN TO CLEAN HAND SANITIZER Gel PLUS
NDC: 71060-070 | Form: GEL
Manufacturer: ONA
Category: otc | Type: HUMAN OTC DRUG LABEL
Date: 20210105

ACTIVE INGREDIENTS: ALCOHOL 70 mL/100 mL
INACTIVE INGREDIENTS: WATER

ONA - ABETTERDAY PERFECT CLEAN HAND SANITIZER GEL

ACTIVE INGREDIENT

Alcohol

INACTIVE INGREDIENT

water, etc

PURPOSE

Antiseptic

keep out of reach of the children

INDICATIONS AND USAGE

Place enough product in your palm to thoroughly spread on both hands and rub into the skin until dry.

Supervise children in the use of this product.

WARNINGS

For external use only.

Flammable.

Keep away from fire or flame.

DOSAGE AND ADMINISTRATION

for external use only